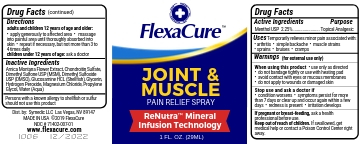 DRUG LABEL: FlexaCure
NDC: 71402-007 | Form: SPRAY
Manufacturer: Symedic LLC
Category: otc | Type: HUMAN OTC DRUG LABEL
Date: 20191014

ACTIVE INGREDIENTS: MENTHOL 2.25 g/100 mL
INACTIVE INGREDIENTS: ARNICA MONTANA FLOWER; DIMETHYL SULFOXIDE; GLYCERIN; MAGNESIUM CHLORIDE; PROPYLENE GLYCOL; HYDROGEN PEROXIDE; CHONDROITIN SULFATE (BOVINE); DIMETHYL SULFATE; GLUCOSAMINE HYDROCHLORIDE; WATER

ACTIVE INGREDIENT

Menthol USP 2.25%

DOSAGE AND ADMINISTRATION

Apply as needed.

WARNINGS

(for external use only)

When using this product

• use only as directed

• do not bandage tightly or use with heating pad

• avoid contact with eyes or mucous membranes

• do not apply to wounds or damaged skin

Stop use and ask a doctor if • condition worsens • symptoms persist for more than 7 days or clear up and occur again within a few days • redness is present • irritation develops

PREGNANCY OR BREAST FEEDING

If pregnant or breast-feeding, ask a health professional before use.

Keep out of reach of children. If swallowed, get medical help or contact a Poison Control Center right away.

INSTRUCTIONS FOR USE

adults and children 12 years of age and older:

• apply generously to affected area • massage into painful area until thoroughly absorbed into skin • repeat if necessary, but not more than 3 to 4 times daily

children under 12 years of age: ask a doctor

INACTIVE INGREDIENT

Arnica Montana Flower Extract, Chondroitin Sulfate, Dimethyl Sulfone USP (MSM), Dimethyl Sulfoxide USP (DMSO), Glucosamine HCL (Shellfish), Glycerin, Hydrogen Peroxide, Magnesium Chloride, Propylene Glycol, Water (Aqua)

OTHER SAFETY INFORMATION

Persons with a known allergy to shellfish or sulfur should not use this product

STATEMENT OF IDENTITY

Dist. by: Symedic LLC Las Vegas, NV 89147

MADE IN USA ©2019 FlexaCure

www.flexacure.com

INDICATIONS AND USAGE

Uses: Temporarily relieves minor pain associated with:

• arthritis • simple backache • muscle strains

• sprains • bruises • cramps

PURPOSE

Topical Analgesic